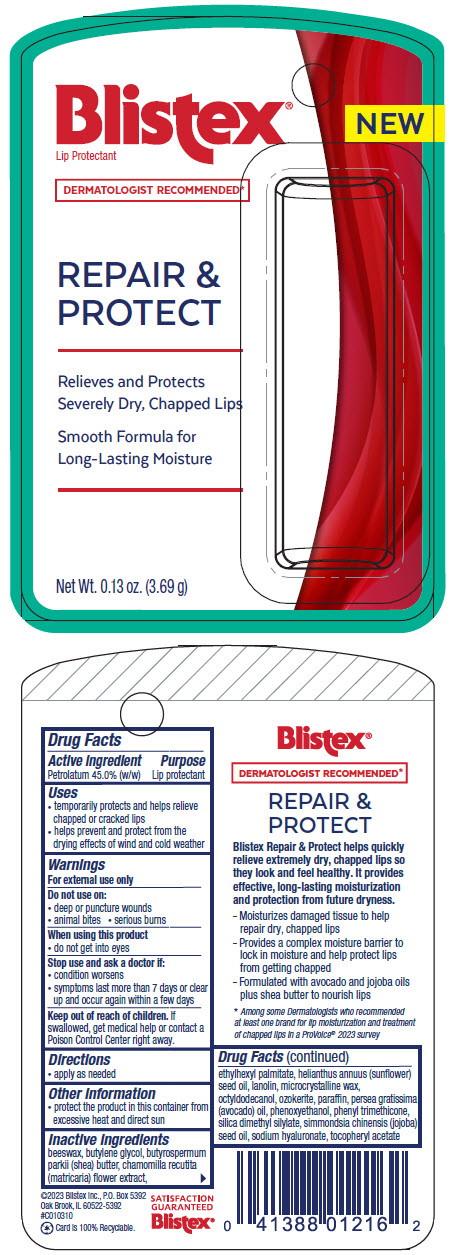 DRUG LABEL: Repair and Protect
NDC: 10157-1189 | Form: STICK
Manufacturer: Blistex Inc.
Category: otc | Type: HUMAN OTC DRUG LABEL
Date: 20250123

ACTIVE INGREDIENTS: PETROLATUM 45 g/100 g
INACTIVE INGREDIENTS: CERESIN; LANOLIN; MICROCRYSTALLINE WAX; OCTYLDODECANOL; PHENYL TRIMETHICONE; YELLOW WAX; SUNFLOWER OIL; CHAMOMILE; ETHYLHEXYL PALMITATE; SILICA DIMETHYL SILYLATE; BUTYLENE GLYCOL; HYALURONATE SODIUM; AVOCADO OIL; JOJOBA OIL; SHEA BUTTER; .ALPHA.-TOCOPHEROL ACETATE; PARAFFIN; PHENOXYETHANOL

Repair & Protect

Drug Facts

Active ingredient

Petrolatum 45.0% (w/w)

Purpose

Lip protectant

Uses

- temporarily protects and helps relieve chapped or cracked lips
- helps prevent and protect from the drying effects of wind and cold weather

Warnings

For external use only

Do not use on

- deep or puncture wounds
- animal bites
- serious burns

When using this product

- do not get into eyes

Stop use and ask a doctor if

- condition worsens
- symptoms last more than 7 days or clear up and occur again within a few days

Keep out of reach of children. If swallowed, get medical help or contact a Poison Control Center right away.

Directions

- apply as needed

Other information

- protect the product in this container from excessive heat and direct sun

Inactive ingredients

beeswax, butylene glycol, butyrospermum parkii (shea) butter, chamomilla recutita (matricaria) flower extract, ethylhexyl palmitate, helianthus annuus (sunflower) seed oil, lanolin, microcrystalline wax, octyldodecanol, ozokerite, paraffin, persea gratissima (avocado) oil, phenoxyethanol, phenyl trimethicone, silica dimethyl silylate, simmondsia chinensis (jojoba) seed oil, sodium hyaluronate, tocopheryl acetate

PRINCIPAL DISPLAY PANEL - 3.69 g Cylinder Blister Pack

Blistex®
NEW
Lip Protectant

DERMATOLOGIST RECOMMENDED*

REPAIR &
PROTECT

Relieves and Protects
Severely Dry, Chapped Lips

Smooth Formula for
Long-Lasting Moisture

Net Wt. 0.13 oz. (3.69 g)